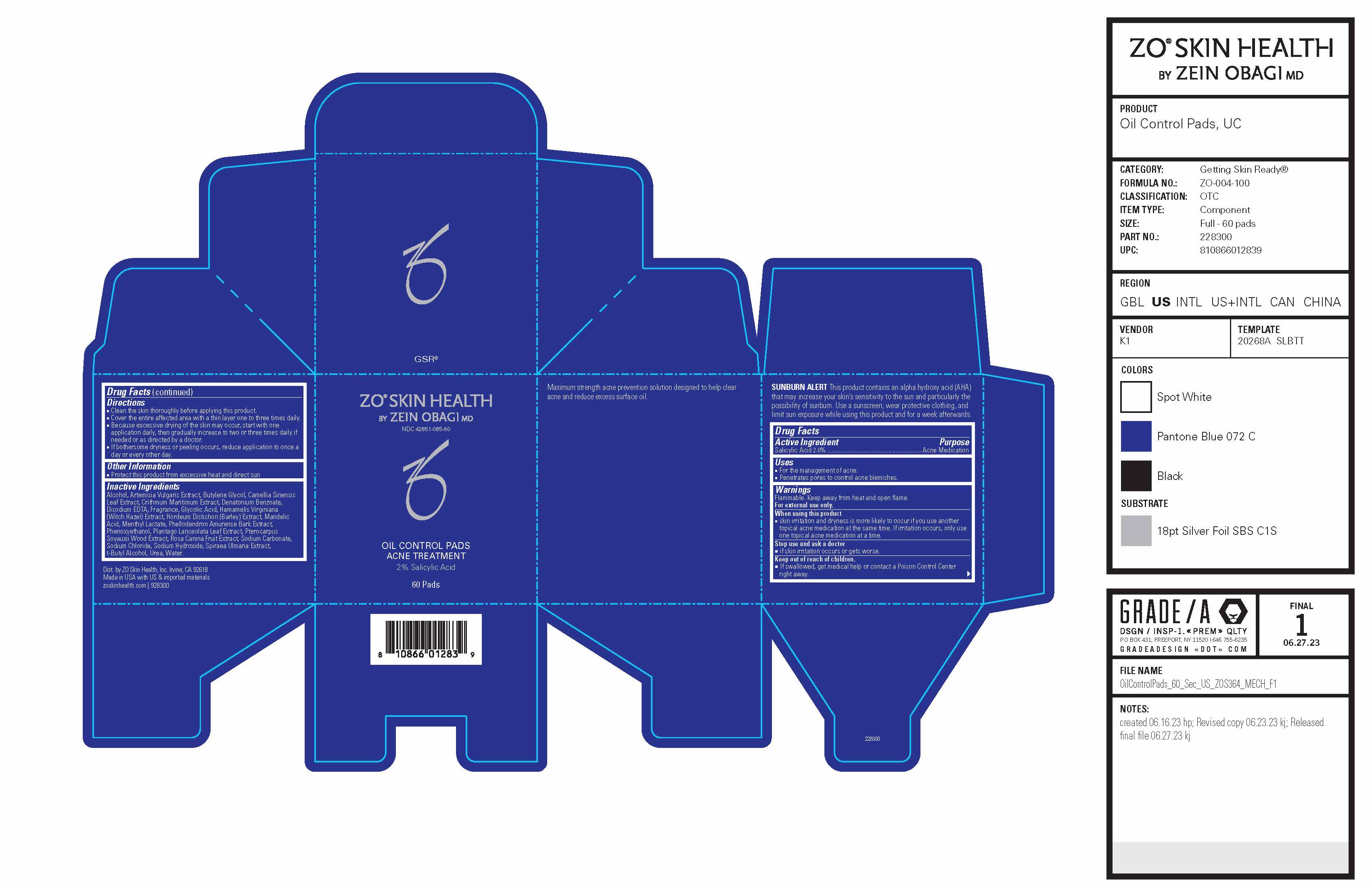 DRUG LABEL: ZO Skin Health Oil Control Pads Acne Treatment
NDC: 42851-085 | Form: PATCH
Manufacturer: ZO Skin Health, Inc.
Category: otc | Type: HUMAN OTC DRUG LABEL
Date: 20241030

ACTIVE INGREDIENTS: SALICYLIC ACID 20 mg/1 mL
INACTIVE INGREDIENTS: UREA; WATER; MANDELIC ACID; PHELLODENDRON AMURENSE BARK; GLYCOLIC ACID; TERT-BUTYL ALCOHOL; DENATONIUM BENZOATE; EDETATE DISODIUM ANHYDROUS; GREEN TEA LEAF; BUTYLENE GLYCOL; CRITHMUM MARITIMUM; SODIUM CHLORIDE; SODIUM CARBONATE; HAMAMELIS VIRGINIANA TOP; MENTHYL LACTATE, (-)-; PLANTAGO LANCEOLATA LEAF; PTEROCARPUS SOYAUXII WOOD; ROSA CANINA FRUIT; ALCOHOL; PHENOXYETHANOL; SODIUM HYDROXIDE

ZO®Skin Health Oil Control Pads Acne Treatment
National Drug Codes: 42851-085-60 and 42851-085-30

Drug Facts

Active ingredient

Salicylic Acid 2.0%

Purpose

Acne Medication

Uses

- For the management of acne.
- Penetrates pores to control acne blemishes.

Warnings

Flammable. Keep away from heat and open flame.

For external use only.

When using this product

- skin irritation and dryness is more likely to occur if you use another topical acne medication at the same time. If irritation occurs, only use one topical acne medication at a time.

Stop use and ask a doctor

- if skin irritation occurs or gets worse.

Keep out of reach of children.

- If swallowed, get medical help or contact a Poison Control Center right away.

Directions

- Clean the skin thoroughly before applying this product.
- Cover the entire affected area with a thin layer one to three times daily.
- Because excessive drying of the skin may occur, start with one application daily, then gradually increase to two or three times daily if needed or as directed by a doctor.
- If bothersome dryness or peeling occurs, reduce application to once a day or every other day.

Other information

- Protect this product from excessive heat and direct sun

Inactive ingredients

Alcohol, Artemisia Vulgaris Extract, Butylene Glycol, Camellia Sinensis Leaf Extract, Crithmum Maritimum Extract, Fragrance, Glycolic Acid, Hamamelis Virginiana (Witch Hazel) Extract, Hordeum Vulgare Seed Extract, Mandelic Acid, Menthyl Lactate, Phenoxyethanol, Phellodendron Amureuse Extract, Plantago Lanceolata Leaf Extract, Pterocarpus Soyauxii Wood Extract, Rosa Canina Fruit Extract, Sodium Hydroxide, Spiraea Ulmaria Extract, Urea, Water.

Dist. by ZO Skin Health, Inc. Irvine, CA 92618

Made in USA with US & imported materials

zoskinhealth.com | 928300

Recent Changes Summary

Contents of Labelling Updates

Capitalized the beginning of all sentences in Directions section.

Deleted from Other Information section: “Read the directions and warnings before use.”

Capitalized sub-heading Active Ingredient

Capitalized active ingredient Salicylic Acid 2.0%

Revised Active Ingredient’s Purpose from “Acne treatment” to “Acne Medication”

Capitalized the beginning of all sentences under Uses section.

Bolded “For external use only.”

Corrected “Stop use and ask a doctor if” to “Stop use and ask a doctor”

Artwork

Uploaded unit carton (SKU no. 928300) to replace previous mark-up’s secondary label (SKU no. 925000).

PRINCIPAL DISPLAY PANEL - 60 Pad Jar Carton

ZO®SKIN HEALTH
BY ZEIN OBAGI MD

NDC 42851-085-60

OIL CONTROL PADS
ACNE TREATMENT

2% Salicylic Acid

60 Pads